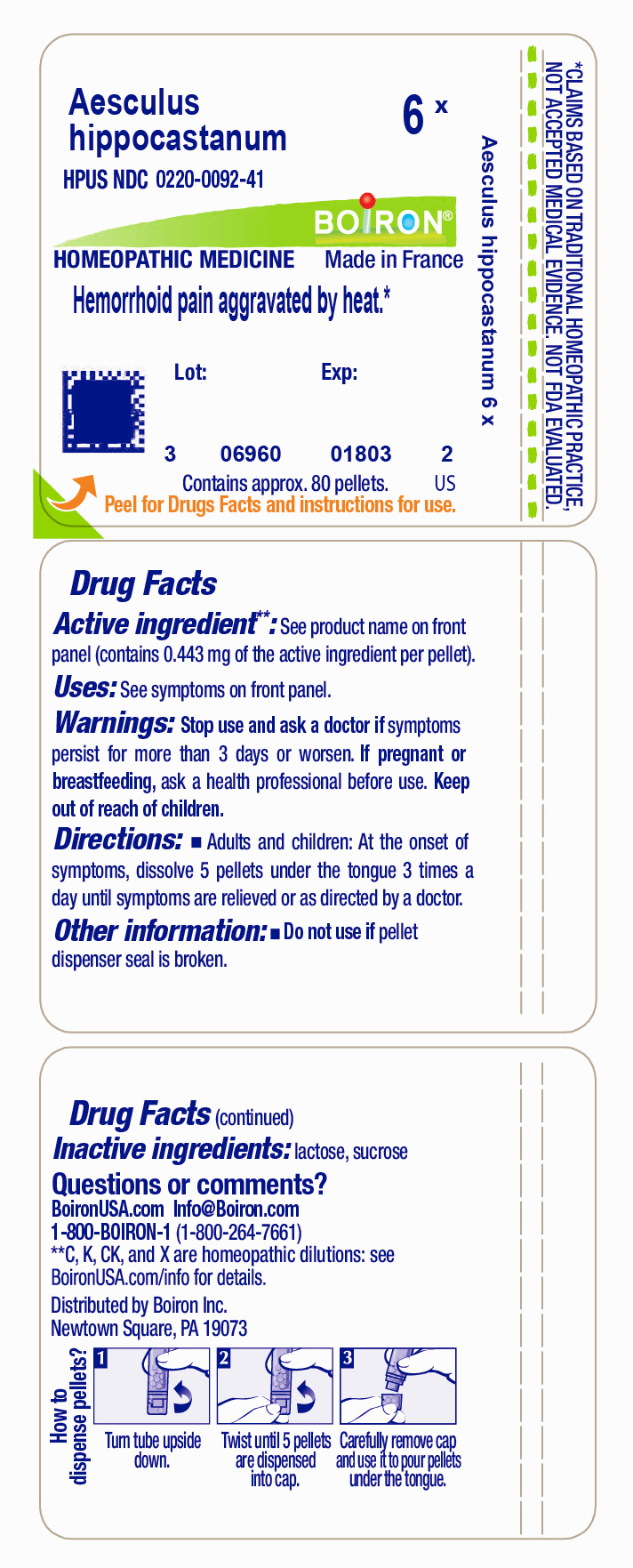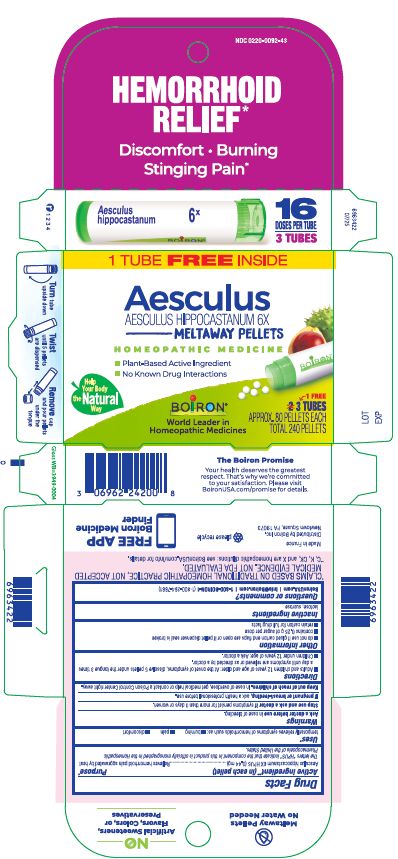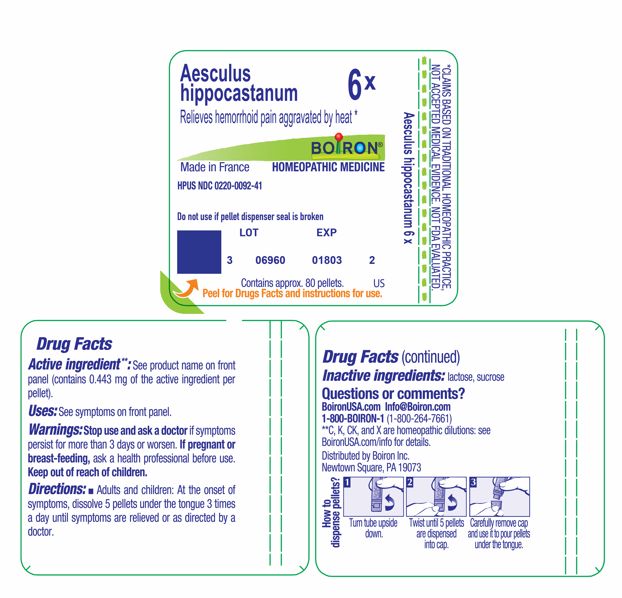 DRUG LABEL: Aesculus hippocastanum
NDC: 0220-0092 | Form: PELLET
Manufacturer: Boiron
Category: homeopathic | Type: HUMAN OTC DRUG LABEL
Date: 20260202

ACTIVE INGREDIENTS: HORSE CHESTNUT 6 [hp_X]/1 1
INACTIVE INGREDIENTS: SUCROSE; LACTOSE

Aesculus hippocastanum 6X

Active ingredient** (in each pellet)

Aesculus hippocastanum 6X HPUS (0.44 mg)

The letters “HPUS” indicate that the component in this product is officially monographed in the Homeopathic Pharmacopoeia of the United States.

Purpose*

Aesculus hippocastanum 6X HPUS (0.44 mg)………..…Relieves hemorrhoid pain aggravated by heat

Uses*

- temporarily relieves symptoms of hemorrhoids such as:
- burning
- pain
- discomfort

Ask a doctor before use in case of bleeding.

Stop use and ask a doctor if symptoms persist for more than 3 days or worsen.

PREGNANCY OR BREAST FEEDING

If pregnant or breast-feeding, ask a health professional before use.

Keep out of reach of children. In case of overdose, get medical help or contact a Poison Control Center right away.

DOSAGE AND ADMINISTRATION

- Adults and children 12 years of age and older: At the onset of symptoms, dissolve 5 pellets under the tongue 3 times a day until symptoms are relieved or as directed by a doctor.
- Children under 12 years of age: Ask a doctor.

INACTIVE INGREDIENT

lactose, sucrose

QUESTIONS

BoironUSA.com

Info@Boiron.com

1-800-BOIRON-1 (1-800-264-7661)

do not use if glued carton end flaps are open or if pellet dispenser seal is broken

contains 0.25 g of sugar per dose

retain carton for full drug facts

Do not use if pellet dispenser seal is broken.

HEMORRHOID RELIEF*

Burning • Swelling

Stinging Pain*

1 TUBE

3 TUBE

APPROX. 80 PELLETS EACH

TOTAL 240 PELLETS

Made in France

Distributed by Boiron Inc.

Newtown Square, PA 19073

How to dispense pellets? Turn tube upside down. Twist until 5 pellets are dispensed Remove cap and pour pellets under the tongue

*CLAIMS BASED ON TRADITIONAL HOMEOPATHIC PRACTICE NOT ACCEPTED MEDICAL EVIDENCE. NOT FDA EVALUATED.
*C,K,CK, and X are homeopathic dilutions: see BoironUSA.com/info for details.